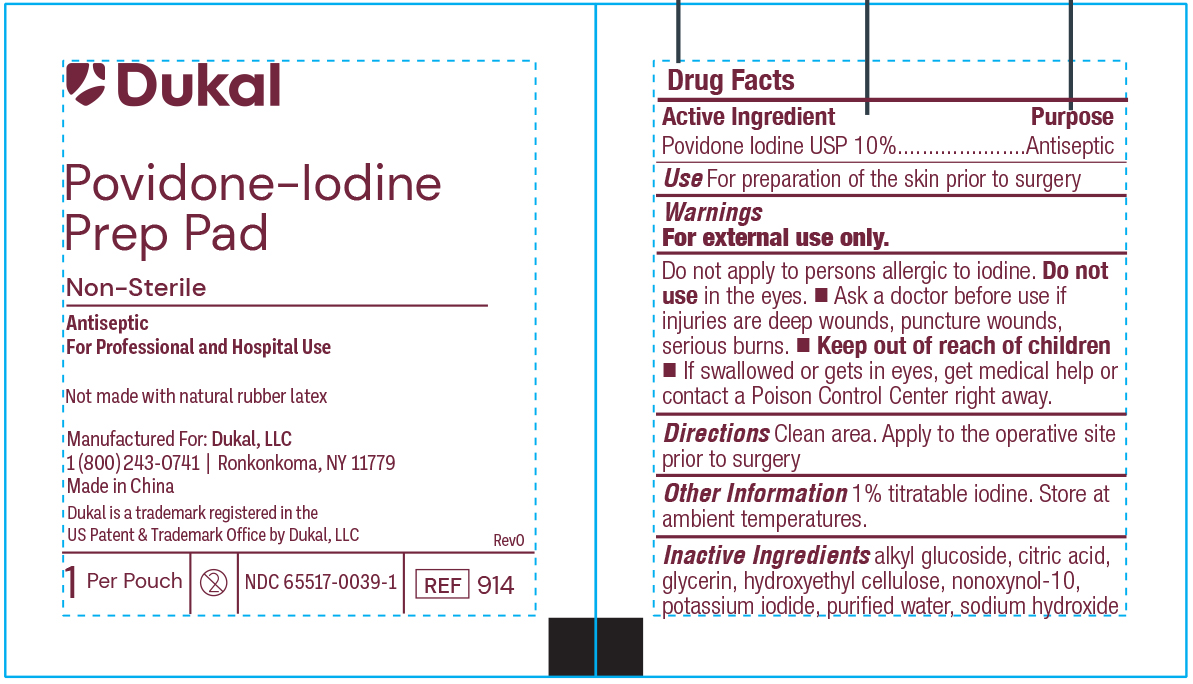 DRUG LABEL: PVP-I  Prep Pads paper-foil
NDC: 65517-0039 | Form: SWAB
Manufacturer: Dukal LLC
Category: otc | Type: HUMAN OTC DRUG LABEL
Date: 20251119

ACTIVE INGREDIENTS: POVIDONE-IODINE 1 g/100 mL
INACTIVE INGREDIENTS: GLYCERIN; HYDROXYETHYL CELLULOSE (2000 MPA.S AT 1%); NONOXYNOL-10; ANHYDROUS CITRIC ACID; SODIUM HYDROXIDE; WATER; C12-20 ALKYL GLUCOSIDE; POTASSIUM IODIDE

65517-0039-1

Active Ingredient:

Povidone Iodine USP 10%

Purpose:

Antiseptic

Use:

For preparation prior to surgery. Helps to reduce bacteria that can potentially cause skin infection.

Warnings:

For external use only.

DO NOT USE

Do not apply to persons allergic to iodine. Do not use in the eyes.

- Ask a doctor before use if injuries are deep wounds, puncture wounds, serious burns.

- Stop use and ask a doctor if irritation and redness develop, condition persists for more than 72 hours, infection occurs.
- Avoid pooling beneath the patient. Prolonged exposure to wet solution may cause skin irritation.

- Keep out of reach of children
- If swallowed or gets in eyes, get medical help or contact a Poison Control Center right away.

Directions:

Clean the area. Apply product to the operative site prior to surgery using pad to prep desired area.

Other Information:

1% titratable iodine, for hospital or professional use only. Store at ambient temperatures.

Inactive Ingredients:

Citric Acid, Glycerin, Sodium Hydroxide, Potassium Iodide, Alkyl Glucoside, Nonoxynol-10, Hydroxyethyl Cellulose and Purified Water.

Principal Display Panel - PVP-I Prep Pads Paper/Foil Pouch Label

Dukal

Povidone-Iodine

Prep Pad

Non-Sterile

Antiseptic

For Professional and Hospital Use

Not Made with Natural Rubber Latex

Manufactured For: Dukal LLC

1(800)243-0741 / Ronkonkoma, NY 11779

Made in China

Dukal is a trademark registered in the

US Patent & Trademark Office by Dukal, LLC

1 Per Pouch / 2 / NDC 65517-0039-1 / REF 914